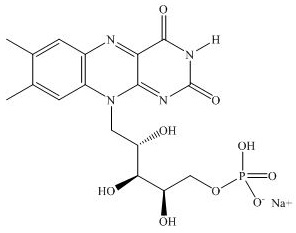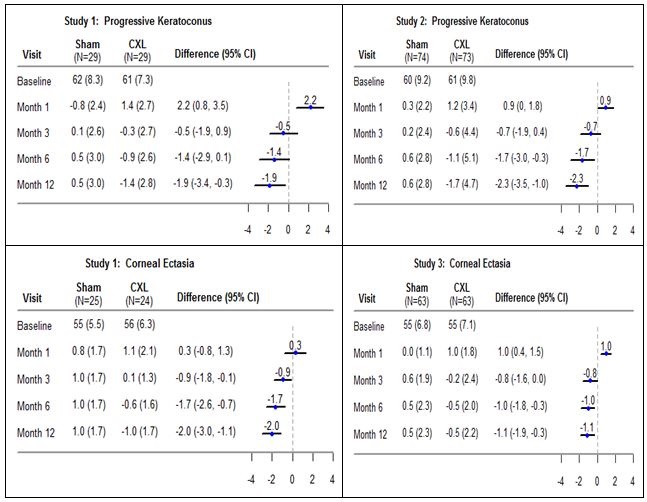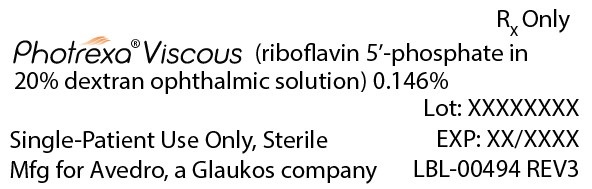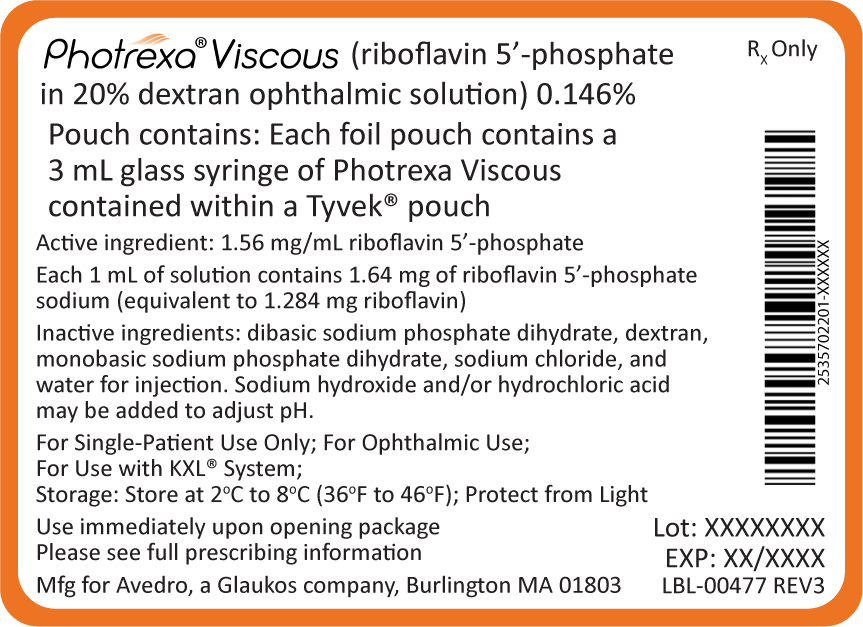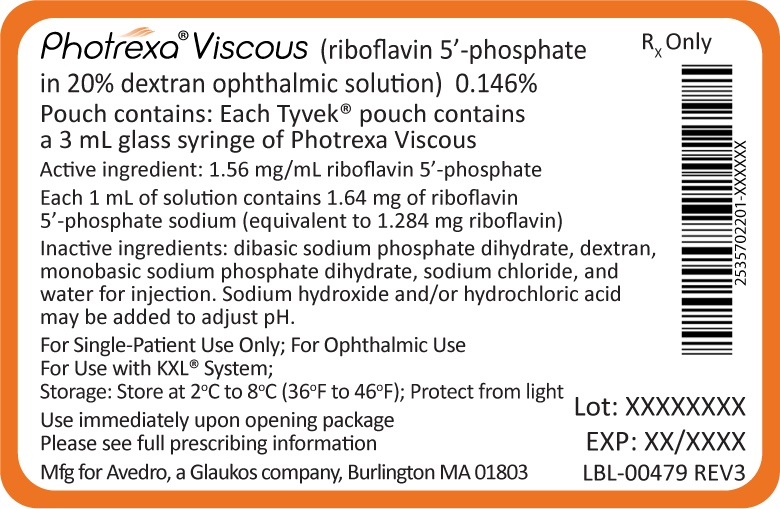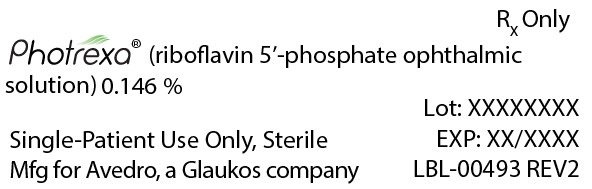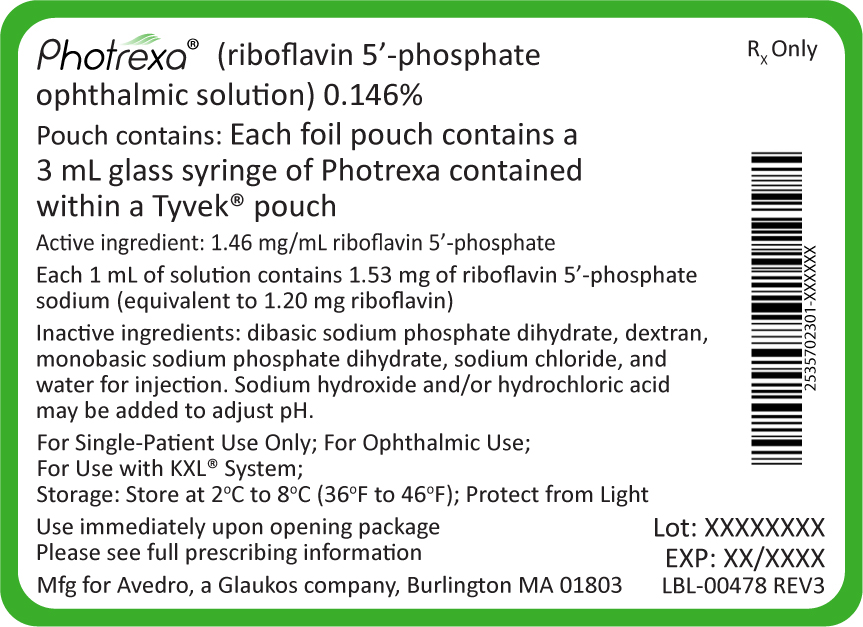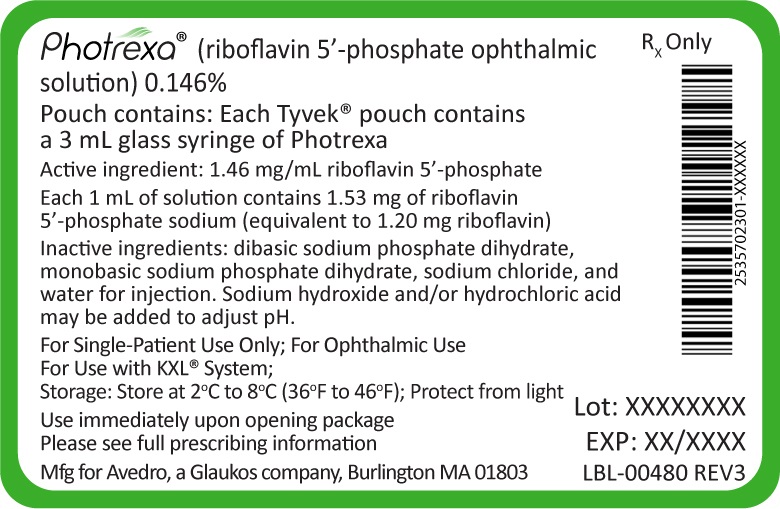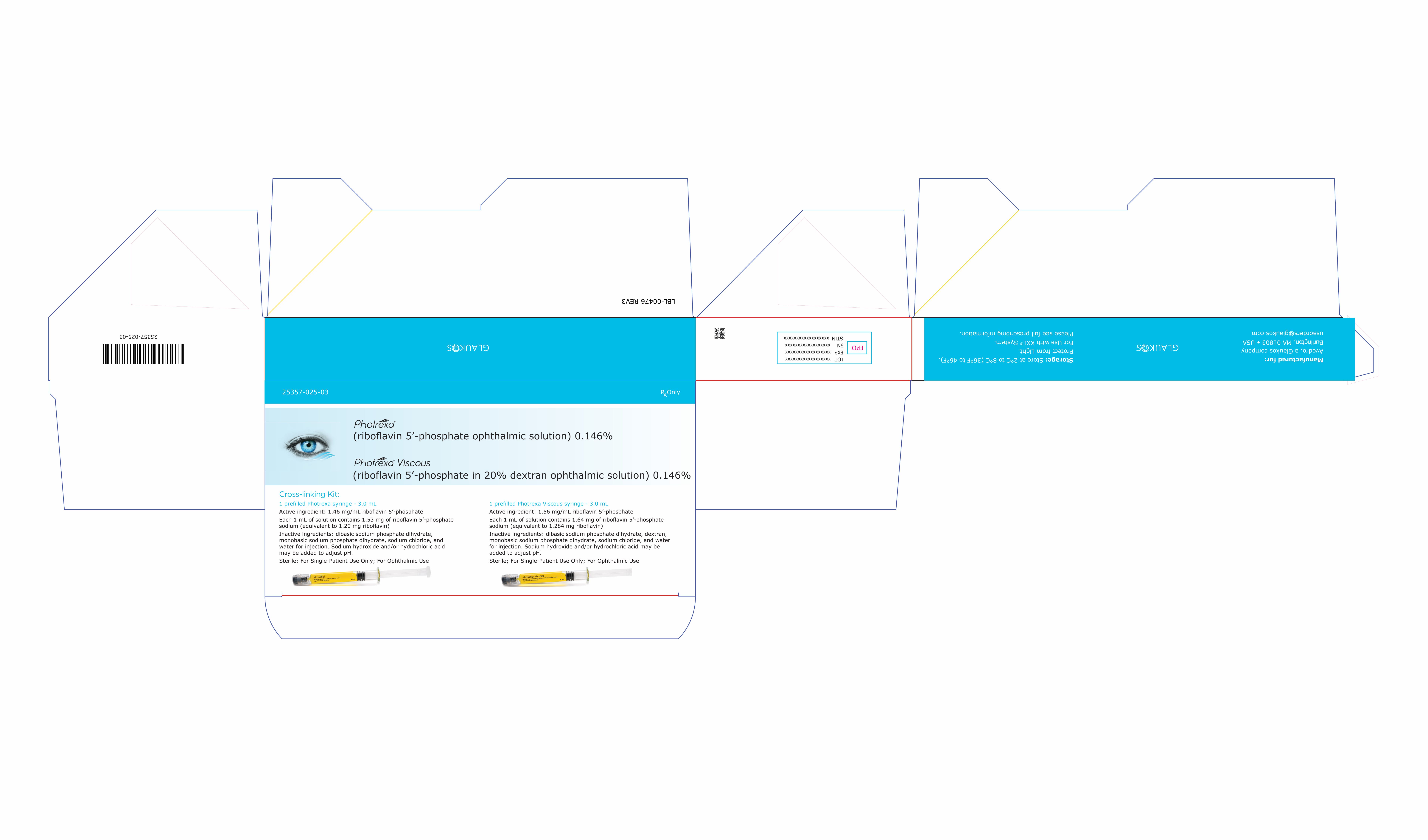 DRUG LABEL: Photrexa Cross-linking Kit
NDC: 25357-025 | Form: KIT | Route: OPHTHALMIC
Manufacturer: Glaukos Corporation
Category: prescription | Type: HUMAN PRESCRIPTION DRUG LABEL
Date: 20251211

ACTIVE INGREDIENTS: RIBOFLAVIN 5'-PHOSPHATE SODIUM ANHYDROUS 1.56 mg/1 mL; RIBOFLAVIN 5'-PHOSPHATE SODIUM ANHYDROUS 1.46 mg/1 mL

HIGHLIGHTS OF PRESCRIBING INFORMATION

These highlights do not include all the information needed to use PHOTREXA® VISCOUS and PHOTREXA® safely and effectively. See full prescribing information for PHOTREXA VISCOUS and PHOTREXA.
PHOTREXA VISCOUS (riboflavin 5’-phosphate in 20% dextran ophthalmic solution) 0.146% for topical ophthalmic use
PHOTREXA (riboflavin 5’-phosphate ophthalmic solution) 0.146% for topical ophthalmic use
For use with the KXL® System
Initial U.S. Approval: 2016

1 INDICATIONS AND USAGE

PHOTREXA VISCOUS and PHOTREXA are photoenhancers indicated for use with the KXL System in corneal collagen cross-linking for the treatment of progressive keratoconus (1.1) and corneal ectasia following refractive surgery (1.2).

2 DOSAGE AND ADMINISTRATION

- Debride the epithelium using standard aseptic technique using topical anesthesia (2).
- Then instill 1 drop of PHOTREXA VISCOUS topically on the eye every 2 minutes for 30 minutes (2).
- After 30 minutes, examine the eye under slit lamp for presence of a yellow flare in the anterior chamber. If flare is not detected, instill 1 drop of PHOTREXA VISCOUS every 2 minutes for an additional 2 to 3 drops and recheck for yellow flare. Repeat as necessary (2).
- Once flare is observed, perform ultrasound pachymetry. If corneal thickness is less than 400 microns, instill 2 drops of PHOTREXA every 5 to 10 seconds until the corneal thickness increases to at least 400 microns (2).
- Irradiation should not be performed unless this 400 micron threshold is met and the yellow flare is seen (2).
- Irradiate the eye for 30 minutes at 3mW/cm^2 using the KXL System as per the instructions in the KXL manual. During irradiation, continue topical instillation of PHOTREXA VISCOUS onto the eye every 2 minutes for the 30 minute irradiation period (2).
- Refer to the KXL Operator’s manual for specific device instructions (2).

3 DOSAGE FORMS AND STRENGTHS

- PHOTREXA VISCOUS in a 3 mL glass syringe containing sterile 1.56 mg/mL riboflavin 5’-phosphate in 20% dextran ophthalmic solution (3.1)
- PHOTREXA in a 3 mL glass syringe containing sterile 1.46 mg/mL riboflavin 5’-phosphate ophthalmic solution (3.2)

4 CONTRAINDICATIONS

None (4)

5 WARNINGS AND PRECAUTIONS

Ulcerative keratitis can occur. Monitor for resolution of epithelial defects (5)

6 ADVERSE REACTIONS

In progressive keratoconus patients, the most common ocular adverse reactions in any CXL-treated eye were corneal opacity (haze), punctate keratitis, corneal striae, corneal epithelium defect, eye pain, reduced visual acuity, and blurred vision (6.1). In corneal ectasia patients, the most common ocular adverse reactions were corneal opacity (haze), corneal epithelium defect, corneal striae, dry eye, eye pain, punctate keratitis, photophobia, reduced visual acuity, and blurred vision (6.1).

To report SUSPECTED ADVERSE REACTIONS, contact Avedro at 1-844-528-3376 or FDA at 1-800-FDA-1088 or www.fda.gov/medwatch.

FULL PRESCRIBING INFORMATION

1 INDICATIONS AND USAGE

PHOTREXA® VISCOUS and PHOTREXA® are indicated for use in corneal collagen cross-linking in combination with the KXL® System for the treatment of

2 DOSAGE AND ADMINISTRATION

Using topical anesthesia, debride the epithelium to a diameter of approximately 9 mm using standard aseptic technique. Post epithelial debridement, instill 1 drop of PHOTREXA VISCOUS topically on the eye every 2 minutes for 30 minutes.

At the end of the 30 minute soaking period, examine the eye under the slit lamp for the presence of a yellow flare in the anterior chamber. If the yellow flare is not detected, instill 1 drop of PHOTREXA VISCOUS every 2 minutes for an additional 2 to 3 drops and recheck for the presence of a yellow flare. This process can be repeated as necessary.

Once the yellow flare is observed, perform ultrasound pachymetry. If corneal thickness is less than 400 microns, instill 2 drops of PHOTREXA every 5 to 10 seconds until the corneal thickness increases to at least 400 microns. Irradiation should not be performed unless this 400 micron threshold is met and the yellow flare is seen.

Irradiate the eye for 30 continuous minutes at 3mW/cm^2 at a wavelength of 365 nm, centered over the cornea, using the KXL System as per the instructions in the KXL manual. During irradiation, continue topical instillation of PHOTREXA VISCOUS onto the eye every 2 minutes for the 30 minute irradiation period.

For topical ophthalmic use. Do not inject.

Single use PHOTREXA VISCOUS and PHOTREXA only. Discard syringe(s) after use.

PHOTREXA VISCOUS and PHOTREXA are for use with the KXL System only.

PLEASE REFER TO THE KXL OPERATOR’S MANUAL FOR SPECIFIC DEVICE INSTRUCTIONS.

3 DOSAGE FORMS AND STRENGTHS

3.1 PHOTREXA VISCOUS

PHOTREXA VISCOUS in a 3 mL glass syringe containing sterile 1.56 mg/mL riboflavin 5’-phosphate in 20% dextran ophthalmic solution for topical administration.

3.2 PHOTREXA

PHOTREXA in a 3 mL glass syringe containing sterile 1.46 mg/mL riboflavin 5’-phosphate ophthalmic solution for topical administration.

4 CONTRAINDICATIONS

None.

5 WARNINGS AND PRECAUTIONS

Ulcerative keratitis can occur. Monitor for resolution of epithelial defects. [See Adverse Reactions (6)].

6 ADVERSE REACTIONS

The following clinically significant adverse reactions are described elsewhere in the labeling:

Ulcerative keratitis [Warnings and Precautions (5)]

6.1 Clinical Trials Experience

Because clinical trials are conducted under widely varying conditions, adverse reaction rates observed in the clinical trials of a drug cannot be directly compared to rates in the clinical trials of another drug and may not reflect the rates observed in practice.

The safety of the corneal collagen cross-linking procedure was evaluated in 3 randomized, parallel-group, open-label, sham-controlled trials; patients were followed up for 12 months. Study 1 enrolled patients with progressive keratoconus or corneal ectasia following refractive surgery. Study 2 enrolled only patients with progressive keratoconus, and Study 3 enrolled only patients with corneal ectasia following refractive surgery. In each study, only one eye of each patient was designated as the study eye. Study eyes were randomized to receive one of the two study treatments (CXL or sham) at the baseline visit and were followed up at Day 1, Week 1, and Months 1, 3, 6, and 12. At Month 3 or later, sham study eyes and non-study eyes had the option of receiving CXL treatment, and were followed-up for 12 months from the time of receiving CXL treatment. Each CXL treated eye received a single course of CXL treatment only.

Safety data were obtained from: 193 randomized CXL study eyes (102 keratoconus, 91 corneal ectasia), 191 control eyes, and 319 nonrandomized CXL non-study eyes (191 keratoconus, 128 corneal ectasia). Overall, 512 eyes (293 keratoconus, 219 corneal ectasia) in 364 patients received CXL treatment.

In progressive keratoconus patients, the most common ocular adverse reactions in any CXL-treated eye were corneal opacity (haze), punctate keratitis, corneal striae, corneal epithelium defect, eye pain, reduced visual acuity, and blurred vision (Table 1).

In corneal ectasia patients, the most common ocular adverse reactions were corneal opacity (haze), corneal epithelium defect, corneal striae, dry eye, eye pain, punctate keratitis, photophobia, reduced visual acuity, and blurred vision. These events are expected sequelae following epithelial corneal debridement and occurred at a higher incidence than observed in control patients, who did not undergo debridement or exposure to UVA light (Table 1).

Adverse events reported in non-study, non-randomized CXL treated were similar in terms of preferred terms and frequency to those seen in randomized study eyes.

The majority of adverse events reported resolved during the first month, while events such as corneal epithelium defect, corneal striae, punctate keratitis, photophobia, dry eye and eye pain, and decreased visual acuity took up to 6 months to resolve and corneal opacity or haze took up to 12 months to resolve. In 1-2% of patients, corneal epithelium defect, corneal edema, corneal opacity and corneal scar continued to be observed at 12 months. In 6% of corneal ectasia patients, corneal opacity continued to be observed at 12 months.

Table 1: Most Common (≥1%) Ocular Adverse Reactions in CXL-Treated Study Eye in the Pooled Randomized Safety Population – N (%)
 | Progressive Keratoconus Studies |  | Corneal Ectasia Studies
Preferred Term | CXL Group (N=102)^1 | Control Group (N=103)^1 | CXL Group (N=91)^1 | Control Group (N=88)^1
Anterior chamber cell | 2 (2) | 0 | 2 (2) | 1 (1)
Anterior chamber flare | 4 (4) | 0 | 5 (6) | 2 (2)
Asthenopia | 1 (1) | 1 (1) | 2 (2) | 0
Blepharitis | 0 | 0 | 0 | 1 (1)
Corneal disorder | 3 (3) | 1 (1) | 3 (3) | 0
Corneal epithelium defect | 24 (24) | 1 (1) | 26 (28) | 3 (3)
Corneal oedema | 3 (3) | 0 | 3 (3) | 0
Corneal opacity^2 | 65 (64) | 9 (9) | 65 (71) | 8 (9)
Corneal striae | 24 (24) | 12 (12) | 8 (9) | 6 (7)
Corneal thinning | 1 (1) | 2 (2) | 0 | 0
Diplopia | 2 (2) | 1 (1) | 1 (1) | 0
Dry eye | 6 (6) | 2 (2) | 13 (14) | 4 (5)
Eye complication associated with device | 2 (2) | 0 | 1 (1) | 0
Eye discharge | 2 (2) | 1 (1) | 0 | 0
Eye oedema | 7 (7) | 0 | 0 | 0
Eye pain | 17 (17) | 3 (3) | 24 (26) | 0
Eye pruritus | 2 (2) | 0 | 0 | 0
Eyelid oedema | 5 (5) | 0 | 5 (6) | 1 (1)
Foreign body sensation in eyes | 15 (15) | 1 (1) | 13 (14) | 2 (2)
Glare | 4 (4) | 1 (1) | 2 (2) | 0
Halo vision | 1 (1) | 0 | 2 (2) | 0
Keratitis | 1 (1) | 0 | 3 (3) | 0
Lacrimation increased | 5 (5) | 0 | 9 (10) | 1 (1)
Meibomian gland dysfunction | 1 (1) | 1 (1) | 3 (3) | 2 (2)
Ocular discomfort | 0 | 0 | 8 (9) | 0
Ocular hyperaemia | 14 (14) | 2 (2) | 7 (8) | 4 (5)
Photophobia | 11 (11) | 0 | 17 (19) | 0
Punctate keratitis | 25 (25) | 8 (8) | 18 (20) | 3 (3)
Vision blurred | 16 (16) | 2 (2) | 15 (17) | 4 (5)
Visual acuity reduced | 10 (10) | 9 (9) | 10 (11) | 1 (1)
Visual impairment | 3 (3) | 2 (2) | 4 (4) | 1 (1)
Vitreous detachment | 2 (2) | 0 | 0 | 0
1) Results are presented as the number (%) of patients with an event from baseline to Month 3.
2) Almost all cases of corneal opacity were reported as haze.

Headache was reported in between 4 to 8% of treated patients.

8 USE IN SPECIFIC POPULATIONS

8.1 Pregnancy

Risk Summary

Animal development and reproduction studies have not been conducted with the PHOTREXA® VISCOUS/PHOTREXA®/KXL® System. Since it is not known whether the corneal collagen cross-linking procedure can cause fetal harm or affect reproduction capacity, it should not be performed on pregnant women.

8.2 Lactation

Risk Summary

There are no data on the presence of PHOTREXA VISCOUS or PHOTREXA in human milk, the effects on the breastfed infant, or the effects on milk production. The developmental and health benefits of breastfeeding should be considered, along with the mother’s clinical need for the PHOTREXA/KXL corneal collagen cross-linking procedure and any potential adverse effects on the breastfed child from the PHOTREXA/KXL corneal collagen cross-linking procedure or from the underlying maternal condition.

8.4 Pediatric Use

The safety and effectiveness of corneal collagen cross-linking has not been established in pediatric patients below the age of 14 years.

8.5 Geriatric Use

No patients enrolled in the clinical studies were 65 years of age or older.

11 DESCRIPTION

PHOTREXA VISCOUS (riboflavin 5’-phosphate in 20% dextran ophthalmic solution) 0.146% and PHOTREXA (riboflavin 5’-phosphate ophthalmic solution) 0.146% are intended for topical ophthalmic administration as part of corneal collagen cross-linking with the KXL System.

PHOTREXA VISCOUS and PHOTREXA are supplied as:

- PHOTREXA VISCOUS in a 3 mL glass syringe containing sterile 1.56 mg/mL riboflavin 5’-phosphate in 20% dextran ophthalmic solution for topical administration.
- PHOTREXA in a 3 mL glass syringe containing sterile 1.46 mg/mL riboflavin 5’-phosphate ophthalmic solution for topical administration.

PHOTREXA VISCOUS (riboflavin 5’-phosphate in 20% dextran ophthalmic solution) 0.146% is a yellow sterile buffered viscous solution containing 1.56 mg/mL riboflavin 5’-phosphate and 20% dextran . The pH of the solution is approximately 7.1 and the osmolality is 284-368 mOsm/kg. Each 1 mL of solution contains 1.64 mg of riboflavin 5’-phosphate sodium (equivalent to 1.284 mg riboflavin). Riboflavin 5’-phosphate sodium is a mixture of the sodium salts of riboflavin, riboflavin monophosphates, and riboflavin diphosphates. The inactive ingredients are dibasic sodium phosphate dihydrate, dextran, monobasic sodium phosphate dihydrate, sodium chloride, and water for injection. Sodium hydroxide and/or hydrochloric acid may be added to adjust pH.

PHOTREXA (riboflavin 5’-phosphate ophthalmic solution) 0.146% is a yellow sterile buffered solution containing 1.46 mg/mL riboflavin 5’-phosphate. The pH of the solution is approximately 7.1 and the osmolality is 157-181 mOsm/kg. Each 1 mL of solution contains 1.53 mg of riboflavin 5’-phosphate sodium (equivalent to 1.20 mg riboflavin). Riboflavin 5’-phosphate sodium is a mixture of the sodium salts of riboflavin, riboflavin monophosphates, and riboflavin diphosphates. The inactive ingredients are dibasic sodium phosphate dihydrate, monobasic sodium phosphate dihydrate, sodium chloride, and water for injection. Sodium hydroxide and/or hydrochloric acid may be added to adjust pH.

The chemical formula for riboflavin 5’-phosphate sodium (Vitamin B2) is C17H20N4NaO9P with a molecular mass of 478.33 g/mol.

Please refer to the KXL System Operator’s Manual for a specific device description and instructions.

12 CLINICAL PHARMACOLOGY

12.1 Mechanism of Action

Riboflavin 5’-phosphate sodium (Vitamin B2) is the precursor of two coenzymes, flavin adenine dinucleotide and flavin mononucleotide, which catalyze oxidation/reduction reactions involved in a number of metabolic pathways.

Under the conditions used for corneal collagen cross-linking, riboflavin 5‘-phosphate functions as a photoenhancer and generates singlet oxygen which is responsible for the cross-linking.

13 NONCLINICAL TOXICOLOGY

13.1. Carcinogenesis, Mutagenesis, Impairment of Fertility

Animal studies have not been conducted to determine the carcinogenic potential of photoexcited riboflavin. Photoexcited riboflavin has been shown to be genotoxic in the Ames Salmonella reverse mutation assay and in the SOS/umu test system.

The genotoxicity of riboflavin, in the absence of photoexcitation has been examined in vitro in bacterial reverse mutation assays, sister chromatid exchange assay, chromosomal aberration assays and in vivo in a mouse micronucleus study. The overall weight of evidence indicates that riboflavin, in the absence of photoexcitation, is not genotoxic.

Animal studies to determine the effects of the PHOTREXA/KXL corneal collagen cross-linking procedure on fertility were not conducted.

14 CLINICAL STUDIES

Three prospective, randomized, parallel-group, open-label, sham-controlled trials were conducted to evaluate the safety and effectiveness of riboflavin ophthalmic solution/UVA irradiation for performing corneal collagen cross-linking. These trials were sham-controlled for the first 3 months and had a total duration of 12 months for safety and efficacy evaluations. Study 1 enrolled 58 patients with progressive keratoconus and 49 patients with corneal ectasia following refractive surgery. Study 2 enrolled 147 patients with progressive keratoconus, and Study 3 enrolled 130 patients with corneal ectasia following refractive surgery. In each study, patients had one eye designated as the study eye and were randomized to receive one of two study treatments (CXL or sham) in their study eye at the baseline visit. The patients were evaluated at Day 1, Week 1, and Months 1, 3, 6, and 12. At Month 3 or later, patients had the option of receiving CXL treatment in both the sham study eyes and non-study eyes and were followed-up for 12 months from the time of receiving CXL treatment.

Approximately 56% and 89% of the sham study eyes in patients with progressive keratoconus received CXL treatment by Month 3 and Month 6, respectively. The average age of keratoconus patients was 33 years. The average baseline Kmax value was 61 diopters. For corneal ectasia patients in Study 1 and Study 3, approximately 60% and 90% of the sham study eyes received CXL treatment by Month 3 and Month 6, respectively. The average age of corneal ectasia patients was 43 years and the average baseline Kmax was 55 diopters. A majority (93%) of the corneal ectasia patients had LASIK only, 5 (3%) patients had photorefractive keratectomy (PRK) only, and 8 (4%) patients had both LASIK and PRK.

In each study, the maximum corneal curvature (Kmax) was assessed at baseline, Months 1, 3, and 12. The CXL-treated eyes showed increasing improvement in Kmax from Month 3 through Month 12 (Figure 1). Progressive keratoconus patients had an average Kmax reduction of 1.4 diopters in Study 1 and 1.7 diopters in Study 2 at Month 12 in the CXL-treated eyes while the sham eyes had an average increase of 0.5 diopter in Study 1 and 0.6 diopter in Study 2 at Month 12; the difference (95% CI) between the CXL and sham groups in the mean change from baseline Kmax were -1.9 (-3.4, -0.3) diopters in Study 1 and -2.3 (-3.5, -1.0) diopters in Study 2.

For corneal ectasia patients, at Month 12, the CXL-treated eyes had an average Kmax reduction of 1.0 diopter in Study 1 and 0.5 diopter in Study 3 while the sham eyes had an average increase of 1.0 diopter in Study 1 and 0.5 diopter in Study 3; the treatment difference between the CXL and sham groups was: -2.0 (-3.0, -1.1) diopters in Study 1 and -1.1 (-1.9, -0.3) diopters in Study 3.

Figure 1: Mean (SD) (Diopter) Baseline Kmax and Change from Baseline Kmax

Post-baseline missing data were imputed using last available Kmax value. For the sham study eyes that received CXL treatment after baseline, the last Kmax measurement recorded prior to receiving CXL treatment was used in the analysis for later time points. In Study 3, four patients in the CXL group had missing baseline Kmax value and were excluded from the analysis.

16 HOW SUPPLIED/STORAGE AND HANDLING

PHOTREXA® VISCOUS and PHOTREXA® are available in the following packaging configuration:

Single-use foil pouches of PHOTREXA® VISCOUS and PHOTREXA® are provided in a kit of two (2): one (1) PHOTREXA® VISCOUS and one (1) PHOTREXA® (NDC 25357-025-03).

Each foil pouch contains a 3 mL glass syringe of PHOTREXA® VISCOUS or PHOTREXA® contained within a Tyvek® pouch.

Kits should be stored at 2°C to 8°C (36°F to 46°F). Care should be taken to minimize exposure of the syringe to light once removed from its protective packaging. Discard syringe after use.

For topical ophthalmic use.

PHOTREXA® VISCOUS and PHOTREXA® should be used with the KXL® System only.

17 PATIENT COUNSELING INFORMATION

- Patients should be advised not to rub their eyes for the first five days after their procedure.
- Patients may be sensitive to light and have a foreign body sensation. Patients should be advised that there may be discomfort in the treated eye and that sunglasses may help with light sensitivity.
- If patients experience severe pain in the eye or any sudden decrease in their vision, they should be advised to contact their physician immediately.
- If the bandage contact lens that was placed on the patient’s eye on the day of treatment falls out or becomes dislodged, the patient should be advised not to replace it and to contact their physician immediately.

PHOTREXA® VISCOUS (riboflavin 5’-phosphate in 20% dextran ophthalmic solution) 0.146%, PHOTREXA® (riboflavin 5’-phosphate ophthalmic solution) 0.146% and the KXL® System are marketed by: Avedro, a Glaukos company, 30 North Avenue, Burlington, MA 01803.

Version:
Issued August 2024

ML-00043 REV3